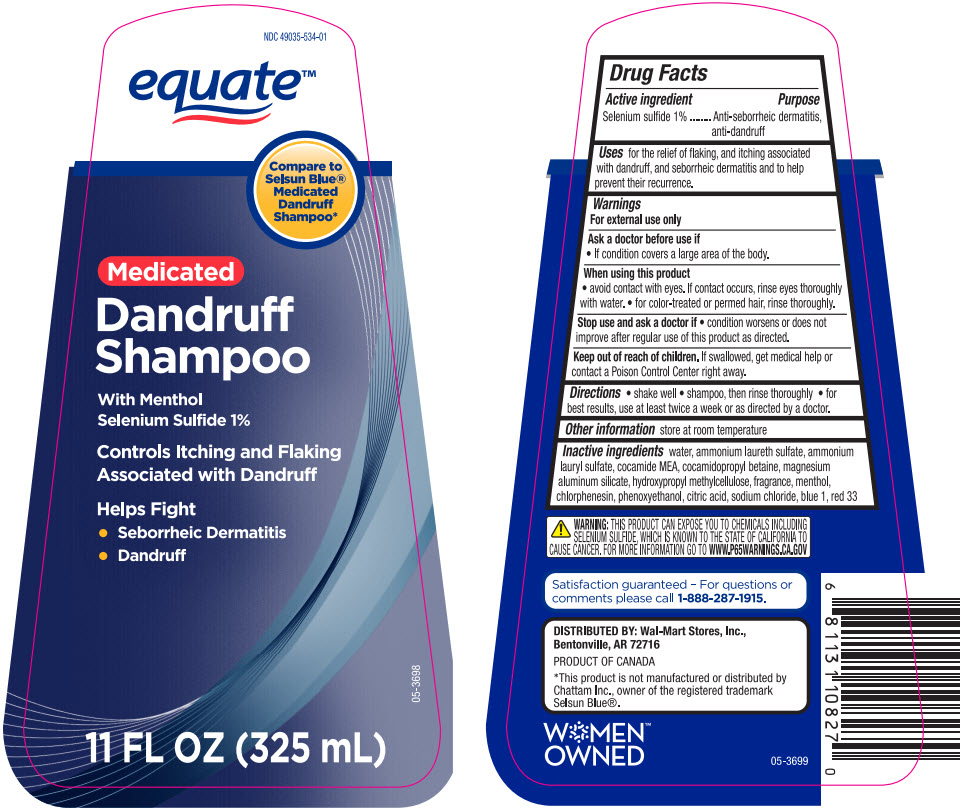 DRUG LABEL: Equate Medicated Dandruff
NDC: 49035-534 | Form: SHAMPOO
Manufacturer: Wal-Mart Stores, Inc.
Category: otc | Type: HUMAN OTC DRUG LABEL
Date: 20241107

ACTIVE INGREDIENTS: Selenium Sulfide 10 mg/1 mL
INACTIVE INGREDIENTS: Water; AMMONIUM LAURETH-5 SULFATE; AMMONIUM LAURYL SULFATE; COCO MONOETHANOLAMIDE; Cocamidopropyl Betaine; Magnesium Aluminum Silicate; HYPROMELLOSE, UNSPECIFIED; MENTHOL, UNSPECIFIED FORM; Chlorphenesin; Phenoxyethanol; CITRIC ACID MONOHYDRATE; Sodium Chloride; FD&C BLUE NO. 1; D&C RED NO. 33

Equate™ Medicated Dandruff Shampoo
Anti-Dandruff

Drug Facts

Active ingredient

Selenium Sulfide 1%

Purpose

Anti-seborrheic dermatitis, anti-dandruff

Use

for the relief of flaking, and itching associated with dandruff, and seborrheic dermatitis and to help prevent their recurrence.

Warnings

For external use only

As a doctor before use if

- condition covers a large area of the body.

When using this product

- avoid contact with the eyes. If contact occurs, rinse eyes thoroughly with water.
- for color-treated or permed hair, rinse thoroughly.

Stop use and ask a doctor if

- condition worsens or does not improve after regular use of this product as directed.

Keep out of reach of children. If swallowed, get medical help or contact a Poison Control Center right away.

Directions

- shake well
- shampoo, then rinse thoroughly
- for best results, use at least twice a week or as directed by a doctor.

Other information

store at room temperature

Inactive ingredients

water, ammonium laureth sulfate, ammonium lauryl sulfate, cocamide MEA, cocamidopropyl betaine, magnesium aluminum silicate, hydroxypropyl methylcellulose, fragrance, menthol, chlorphenesin, phenoxyethanol, citric acid, sodium chloride, blue 1, red 33

QUESTIONS

Satisfaction guaranteed - For questions or comments please call 1-888-287-1915.

DISTRIBUTED BY: Wal-Mart Stores, Inc.,
Bentonville, AR 72716

PRINCIPAL DISPLAY PANEL - 325 mL Bottle Label

NDC 49035-534-01

equate™

Compare to
Selsun Blue®
Medicated
Dandruff
Shampoo*

Medicated

Dandruff
Shampoo

With Menthol
Selenium Sulfide 1%

Controls Itching and Flaking
Associated with Dandruff

Helps Fight

- Seborrheic Dermatitis
- Dandruff

11 FL OZ (325 mL)

05-3698